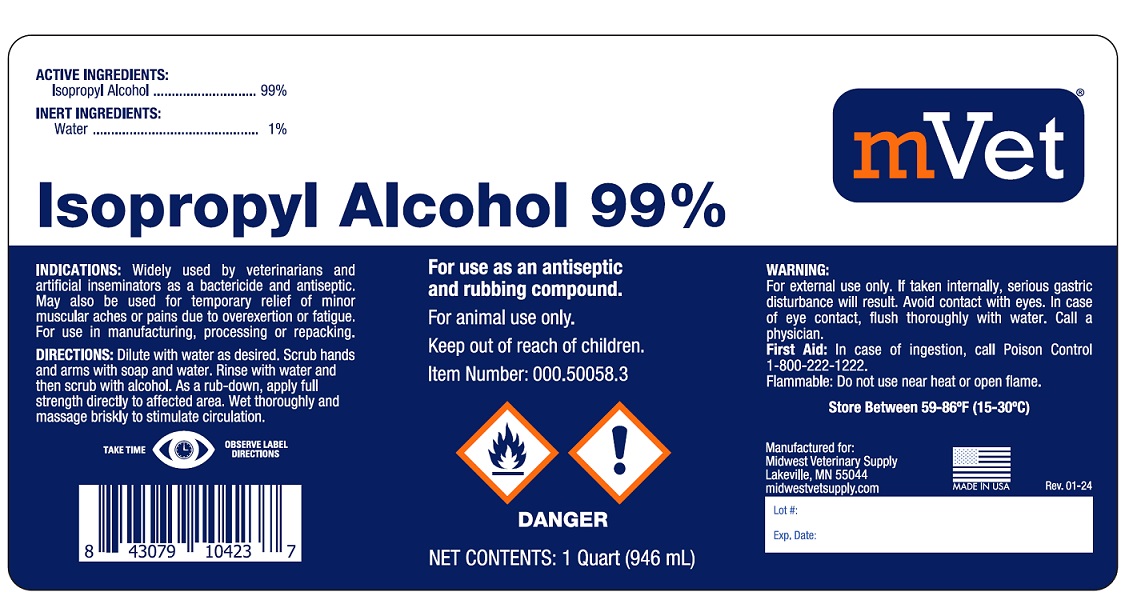 DRUG LABEL: ISOPROPYL ALCOHOL
NDC: 86223-033 | Form: LIQUID
Manufacturer: Midwest Veterinary Supply, Inc
Category: animal | Type: OTC ANIMAL DRUG LABEL
Date: 20250508

ACTIVE INGREDIENTS: ISOPROPYL ALCOHOL 99 mL/100 mL
INACTIVE INGREDIENTS: WATER 1 mL/100 mL

INDICATIONS AND USAGE

Isopropyl Alcohol 99%

ACTIVE INGREDIENTS:

Isopropyl Alcohol ...............99%

INACTIVE INGREDIENTS:

Water ............................. 1%

For use as an antiseptic and rubbing compound.

For animal use only.

Keep out of reach of children.

INDICATIONS: Widely used by veterinarians and artificial inseminators as a bactericide and antiseptic. May also be used for temporary relief of minor muscular aches or pains due to overexertion or fatigue. For use in manufacturing processing, or repacking.

DIRECTIONS: Dilute with water as desired. Scrub hands and arms with soap and water. Rinse with water and then scrub with alcohol. As a rub- down, apply full strength directly to affected area. Wet thoroughly and massage briskly to stimulate circulation.

WARNING: For external use only. If taken internally, serious gastric disturbance will result. Avoid contact with eyes. In case of eye contact, flush thoroughly with water. Call a physician.

First Aid: In case of ingestion, call Poison Control 1-800-222-1222.

Flammable: Do not use near heat or open flames.

Store Between 59-86°F (15-30°C)

Manufactured for:

Midwest Veterinary Supply

Lakeville, MN 55044

midwestvetsupply.com

MADE IN USA